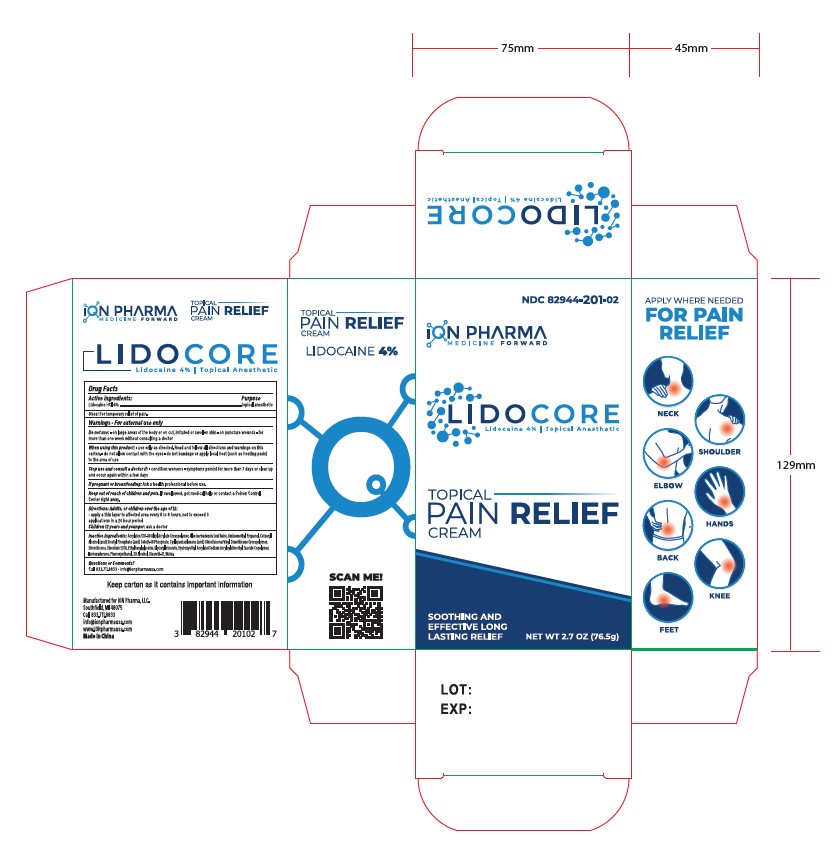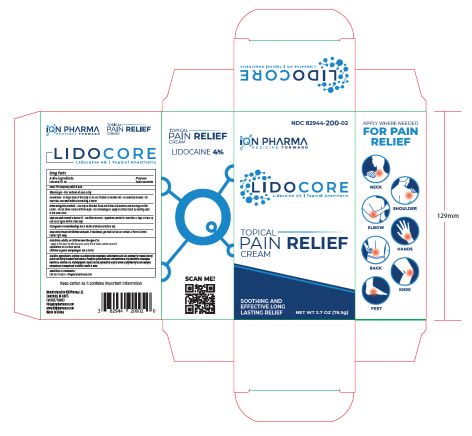 DRUG LABEL: Lidocore
NDC: 82944-201 | Form: CREAM
Manufacturer: iON Pharma, LLC
Category: otc | Type: HUMAN OTC DRUG LABEL
Date: 20250205

ACTIVE INGREDIENTS: LIDOCAINE HYDROCHLORIDE ANHYDROUS 3.1 g/76.5 g
INACTIVE INGREDIENTS: GLYCERYL 1-STEARATE; ETHYLHEXYLGLYCERIN; STEARETH-21; DIMETHICONE/VINYL DIMETHICONE CROSSPOLYMER (SOFT PARTICLE); DIMETHICONE 350; ACRYLATES/C10-30 ALKYL ACRYLATE CROSSPOLYMER (60000 MPA.S); ALCOHOL 95%; ALOE VERA LEAF; PHENOXYETHANOL; CYCLOMETHICONE 5; HYDROXYETHYL ACRYLATE/SODIUM ACRYLOYLDIMETHYL TAURATE COPOLYMER (100000 MPA.S AT 1.5%); EDETATE DISODIUM ANHYDROUS; WATER; AMINOMETHYLPROPANOL; CETETH-10 PHOSPHATE; ISOHEXADECANE; CETOSTEARYL ALCOHOL; DIHEXADECYL PHOSPHATE

Lidocore Cream (Lidocaine 4%)

drug facts Active ingredients

Drug Facts
Active ingredients: Purpose
Lidocaine HCI 4% Topical anesthetic

Uses

Uses: For temporary relief of pain.

Do not use section

Do not use on large areas of the body or on cut, irritated or swollen skin, on puncture wounds for more than one week without consulting a doctor

when using this product section

When using this product use only as directed. Read and follow all directions and warnings on this
carton. Do not allow contact with the eyes, do not bandage or apply local heat (such as heating pads) to the area of use

Stop use section

Stop use and consult a doctor if condition worsens, symptoms persist for more than 7 days or clear up
and occur again within a few days

If pregnant or breastfeeding section

If pregnant or breastfeeding, ask a health professional before use.

Keep out of reach of children and pets section

Keep out of reach of children and pets. If swallowed, get medical help or contact a Poison Control
Center right away.

Directions section

Directions: Adults, or children over the age of 12, apply a thin layer to affected area every 6 to 8 hours, not to exceed 3 applications in a 24 hour period. Children 12 years and younger ask a doctor

INACTIVE INGREDIENT

Inactive Ingredients: Acrylates/C10-30 Alkyl Acrylate Crosspolymer, Aloe barbadensis Leaf Juice, Aminomethyl Propanol, Cetearyl
Alcohol (and) Dicetyl Phosphate (and) Ceteth-10 Phosphate, Cyclopentasiloxane (and) Dimethicone/Vinyl Dimethicone Crosspolymer,
Dimethicone, Disodium EDTA, Ethylhexylglycerin, Glyceryl stearate, Hydroxyethyl Acrylate/Sodium Acryloyldimethyl Taurate Copolymer, Isohexadecane, Phenoxyethanol, SD Alcohol, Steareth-21, Water.

Questions or comments section

Questions or Comments?
Call 833.711.8833 , info@ionpharmausa.com